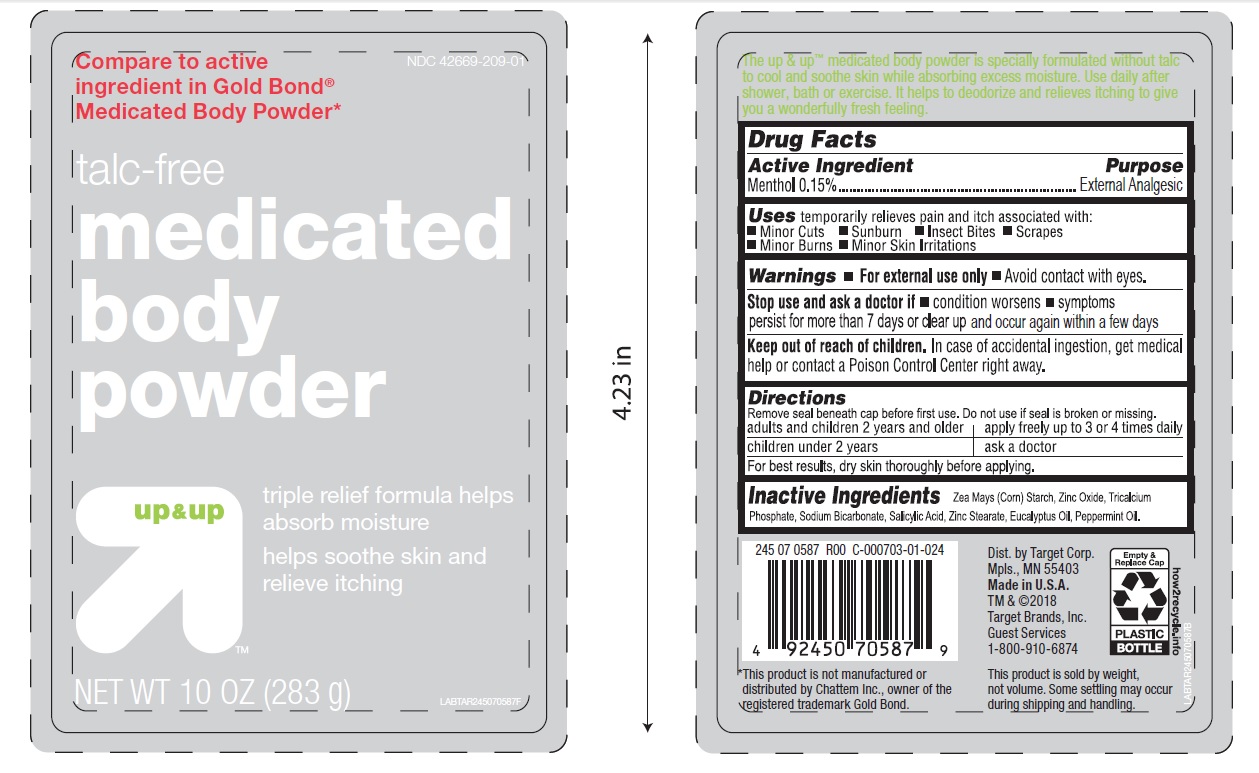 DRUG LABEL: talc-free medicated body
NDC: 42669-209 | Form: POWDER
Manufacturer: Davion, Inc
Category: otc | Type: HUMAN OTC DRUG LABEL
Date: 20251229

ACTIVE INGREDIENTS: MENTHOL 0.15 g/100 g
INACTIVE INGREDIENTS: STARCH, CORN; ZINC OXIDE; TRICALCIUM PHOSPHATE; SODIUM BICARBONATE; SALICYLIC ACID; EUCALYPTUS OIL; ZINC STEARATE; PEPPERMINT OIL

talc-free medicated body powder

Active Ingredient

Menthol 0.15%

Purpose

External Analgesic

Uses

Temporary relief of pain and itch associated with:

- minor cuts
- sunburn
- insect bites
- scrapes
- minor burns
- minor skin irritations

Warning

- For external use only
- Avoid contact with eyes

Stop use and ask a doctor if

- condition worsens
- symptoms persist for more than 7 days or clear up and occur again within few days

Keep out of reach of children

In case of accidental ingestion, get medical help or contact a poison control center right away.

Directions

Remove seal beneath cap before first use. Do not use if seal is broken or missing.

- adults and children 2 years and older - apply freely upto 3 or 4 times daily
- children under 2 years - ask a doctor

For best results, dry skin throughly before applying

Inactive ingredients

Zea Mays (Corn) Starch, zinc oxide, Tricalcium Phosphate, Sodium Bicarbonate, salicylic acid, zinc stearate, Eucalyptus oil, Peppermint Oil

PRINCIPAL DISPLAY PANEL

NDC 42669-209-01

Compare to active ingredient in Gold Bond® Medicated Body Powder*

talc-free medicated body powder

triple relief formulahelps absorb moisture

helps soothe skin and relieves itching

NET WT 10oz (283 g)